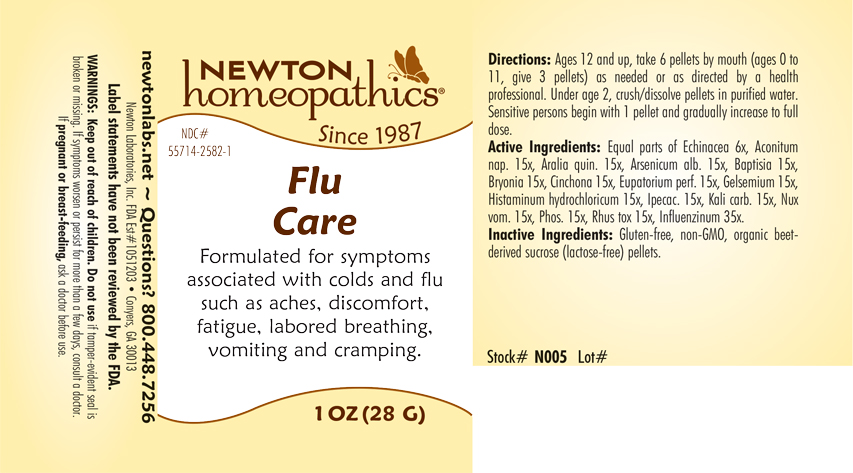 DRUG LABEL: Flu Care
NDC: 55714-2582 | Form: PELLET
Manufacturer: Newton Laboratories, Inc.
Category: homeopathic | Type: HUMAN OTC DRUG LABEL
Date: 20240214

ACTIVE INGREDIENTS: INFLUENZA A VIRUS 35 [hp_X]/1 g; INFLUENZA B VIRUS 35 [hp_X]/1 g; HISTAMINE DIHYDROCHLORIDE 15 [hp_X]/1 g; ACONITUM NAPELLUS 15 [hp_X]/1 g; AMERICAN GINSENG 15 [hp_X]/1 g; ARSENIC TRIOXIDE 15 [hp_X]/1 g; BAPTISIA TINCTORIA 15 [hp_X]/1 g; BRYONIA ALBA ROOT 15 [hp_X]/1 g; CINCHONA OFFICINALIS BARK 15 [hp_X]/1 g; EUPATORIUM PERFOLIATUM FLOWERING TOP 15 [hp_X]/1 g; GELSEMIUM SEMPERVIRENS ROOT 15 [hp_X]/1 g; IPECAC 15 [hp_X]/1 g; POTASSIUM CARBONATE 15 [hp_X]/1 g; STRYCHNOS NUX-VOMICA SEED 15 [hp_X]/1 g; PHOSPHORUS 15 [hp_X]/1 g; TOXICODENDRON PUBESCENS LEAF 15 [hp_X]/1 g; ECHINACEA, UNSPECIFIED 6 [hp_X]/1 g
INACTIVE INGREDIENTS: SUCROSE

Flu 2582P

INDICATIONS & USAGE SECTION

Formulated for symptoms associated with colds and flu such as aches, discomfort, fatigue, labored breathing, vomiting and cramping.

DOSAGE & ADMINISTRATION SECTION

Directions: Ages 12 and up, take 6 pellets by mouth (ages 0 to 11, give 3 pellets) as needed or as directed by a health professional. Under age 2, crush/dissolve pellets in purfied water. Sensitive persons begin with 1 pellet and gradually increase to full dose.

OTC - ACTIVE INGREDIENT SECTION

Equal parts of Echinacea 6x, Aconitum napellus 15x, Aralia quinquefolia 15x, Arsenicum album 15x, Baptisia tinctoria 15x, Bryonia 15x, Cinchona 15x, Eupatorium perf. 15x, Gelsemium 15x, Histaminum hydrochloricum 15x, Ipecac. 15x, Kali carb. 15x, Nux vom. 15x, Phos. 15x, Rhus tox. 15x, Influenzinum 35x.

OTC - PURPOSE SECTION

Formulated for symptoms associated with colds and flu such as aches, discomfort, fatigue, labored breathing, vomiting and cramping.

INACTIVE INGREDIENT SECTION

Inactive Ingredients: Gluten-free, non-GMO, organic beet-derived sucrose (lactrose-free) pellets.

QUESTIONS SECTION

newtonlabs.net – Questions? 800.448.7256

Newton Laboratories, Inc. FDA Est # 1051203 - Conyers, GA 30013

WARNINGS SECTION

WARNINGS: Keep out of reach of children. Do not use if tamper-evident seal is broken or missing. If symptoms worsen or persist for more than a few days, consult a doctor. If pregnant or breast-feeding, ask a doctor before use.

OTC - PREGNANCY OR BREAST FEEDING SECTION

If pregnant or breast-feeding, ask a doctor before use.

OTC - KEEP OUT OF REACH OF CHILDREN SECTION

Keep out of reach of children.